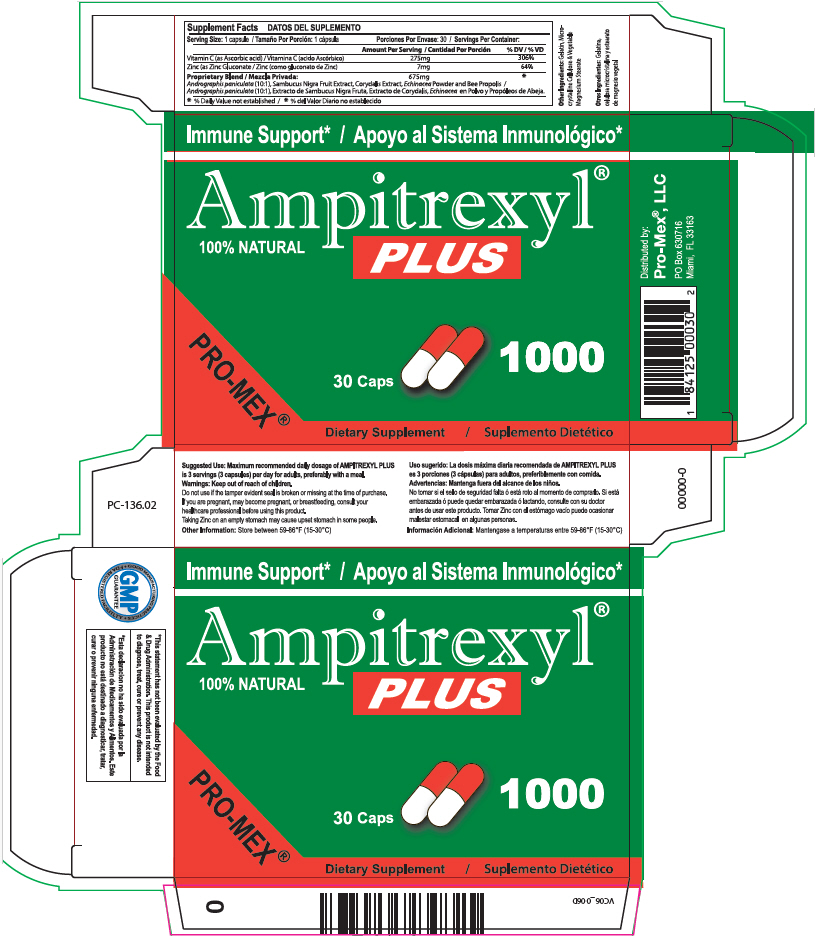 DRUG LABEL: AMPITREXYL PLUS
NDC: 58988-1831 | Form: CAPSULE
Manufacturer: ProMex LLC
Category: other | Type: DIETARY SUPPLEMENT
Date: 20250701

ACTIVE INGREDIENTS: ASCORBIC ACID 275 mg/1 1; ZINC GLUCONATE 7 mg/1 1
INACTIVE INGREDIENTS: ANDROGRAPHIS PANICULATA WHOLE; EUROPEAN ELDERBERRY; DICENTRA CANADENSIS ROOT; ECHINACEA, UNSPECIFIED; PROPOLIS WAX; GELATIN, UNSPECIFIED; MICROCRYSTALLINE CELLULOSE; MAGNESIUM STEARATE

AMPITREXYL® PLUS

STATEMENT OF IDENTITY

Supplement Facts
Serving Size: 1 capsule | Servings Per Container:
 | Amount Per Serving | % DV
Vitamin C (as Ascorbic acid) | 275mg | 306%
Zinc (as Zinc Gluconate) | 7mg | 64%
Proprietary Blend: | 675mg | [% Daily Value not established]
Andrographis paniculata (10:1), Sambucus Nigra Fruit Extract, Corydalis Extract, Echinacea Powder and Bee Propolis

Other Ingredients: Gelatin, Microcrystalline Cellulose & Vegetable Magnesium Stearate

Suggested Use

Maximum recommended daily dosage of AMPITREXYL PLUS is 3 servings (3 capsules) per day for adults, preferably with a meal.

Warnings

Keep out of reach of children.

Do not use if the tamper evident seal is broken or missing at the time of purchase.

If you are pregnant, may become pregnant, or breastfeeding, consult your healthcare professional before using this product.

Taking Zinc on an empty stomach may cause upset stomach in some people.

Other Information

Store between 59-86°F (15-30°C)

HEALTH CLAIM

*This statement has not been evaluated by the Food & Drug Administration. This product is not intended to diagnose, treat, cure or prevent any disease.

HEALTH CLAIM

Distributed by:
Pro-Mex®, LLC
PO Box 630716
Miami, FL 33163

PRINCIPAL DISPLAY PANEL - 30 Capsule Blister Pack Carton

Immune Support*

Ampitrexyl®
100% NATURAL
PLUS

PRO-MEX®

30 Caps
1000

Dietary Supplement